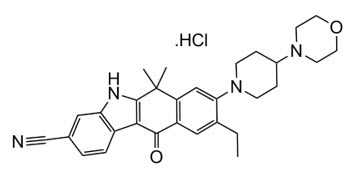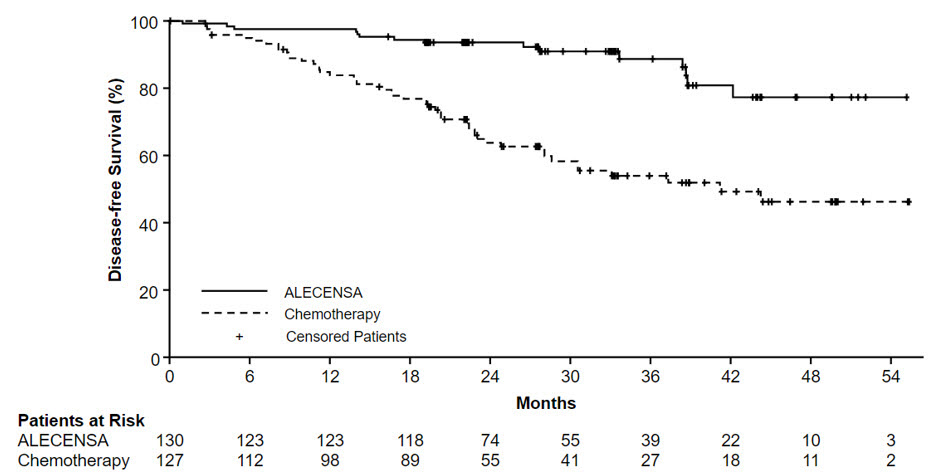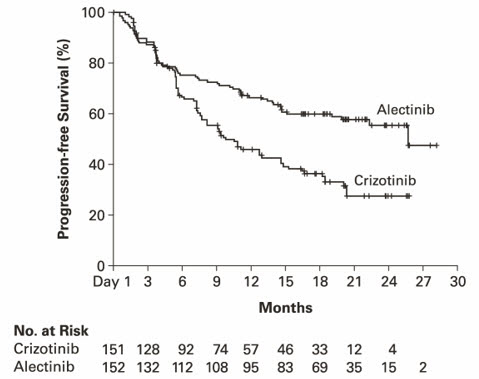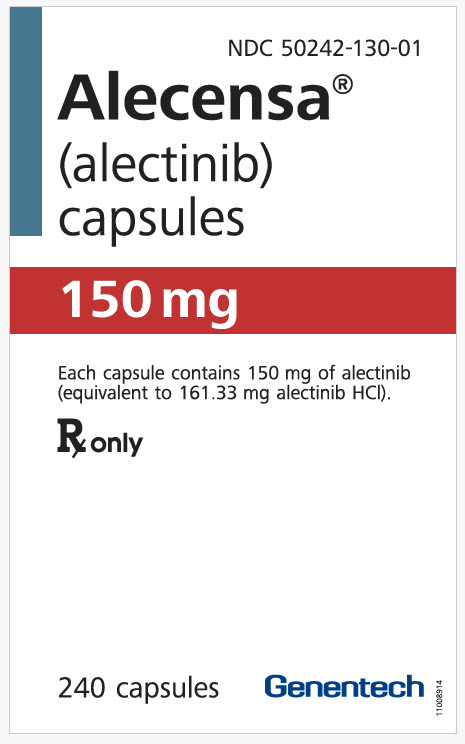 DRUG LABEL: ALECENSA
NDC: 50242-130 | Form: CAPSULE
Manufacturer: Genentech, Inc.
Category: prescription | Type: HUMAN PRESCRIPTION DRUG LABEL
Date: 20251215

ACTIVE INGREDIENTS: ALECTINIB HYDROCHLORIDE 150 mg/1 1
INACTIVE INGREDIENTS: LACTOSE MONOHYDRATE; HYDROXYPROPYL CELLULOSE (1600000 WAMW); SODIUM LAURYL SULFATE; CARBOXYMETHYLCELLULOSE CALCIUM; MAGNESIUM STEARATE; CARRAGEENAN; POTASSIUM CHLORIDE; TITANIUM DIOXIDE; CARNAUBA WAX; STARCH, CORN; HYPROMELLOSE, UNSPECIFIED; FERRIC OXIDE RED; FERRIC OXIDE YELLOW; FD&C BLUE NO. 2; SHELLAC; GLYCERYL OLEATE

HIGHLIGHTS OF PRESCRIBING INFORMATION

These highlights do not include all the information needed to use ALECENSA safely and effectively. See full prescribing information for ALECENSA.
ALECENSA® (alectinib) capsules, for oral use
Initial U.S. Approval: 2015

RECENT MAJOR CHANGES

Indications and Usage (1.1) | 04/2024
Dosage and Administration (2.1, 2.2, 2.3) | 04/2024
Warnings and Precautions (5) | 04/2024

1 INDICATIONS AND USAGE

ALECENSA is a kinase inhibitor indicated for:

- adjuvant treatment in adult patients following tumor resection of anaplastic lymphoma kinase (ALK)-positive non-small cell lung cancer (NSCLC) (tumors ≥ 4 cm or node positive) as detected by an FDA-approved test. (1.1)
- treatment of adult patients with ALK-positive metastatic NSCLC as detected by an FDA-approved test. (1.2)

2 DOSAGE AND ADMINISTRATION

600 mg orally twice daily. Administer ALECENSA with food. (2.2)

3 DOSAGE FORMS AND STRENGTHS

Capsules: 150 mg (3)

4 CONTRAINDICATIONS

None. (4)

5 WARNINGS AND PRECAUTIONS

- Hepatotoxicity: Monitor liver laboratory tests every 2 weeks during the first 3 months of treatment, then once a month and as clinically indicated, with more frequent testing in patients who develop transaminase and bilirubin elevations. In case of severe ALT, AST, or bilirubin elevations, withhold, then reduce dose, or permanently discontinue ALECENSA. (2.4, 5.1)
- Interstitial Lung Disease (ILD)/Pneumonitis: Immediately withhold ALECENSA in patients diagnosed with ILD/pneumonitis and permanently discontinue if no other potential causes of ILD/pneumonitis have been identified. (2.4, 5.2)
- Renal Impairment: Withhold ALECENSA for severe renal impairment, then resume ALECENSA at reduced dose upon recovery or permanently discontinue (2.4, 5.3).
- Bradycardia: Monitor heart rate and blood pressure regularly. If symptomatic, withhold ALECENSA then reduce dose, or permanently discontinue. (2.4, 5.4)
- Severe Myalgia and Creatine Phosphokinase (CPK) Elevation: Assess CPK every 2 weeks during the first month of treatment and in patients reporting unexplained muscle pain, tenderness, or weakness. In case of severe CPK elevations, withhold, then resume or reduce dose. (2.4, 5.5)
- Hemolytic Anemia: If hemolytic anemia is suspected, withhold ALECENSA. If hemolytic anemia is confirmed, consider resuming at a reduced dose upon resolution or permanently discontinue. (5.6)
- Embryo-Fetal Toxicity: ALECENSA can cause fetal harm. Advise females of reproductive potential of the potential risk to a fetus and to use effective contraception. (5.7, 8.1, 8.3)

6 ADVERSE REACTIONS

The most common adverse reactions (incidence ≥20%) were hepatotoxicity, constipation, fatigue, myalgia, edema, rash and cough. (6.1)

To report SUSPECTED ADVERSE REACTIONS, contact Genentech at 1-888-835-2555 or FDA at 1-800-FDA-1088 or www.fda.gov/medwatch.

8 USE IN SPECIFIC POPULATIONS

Lactation: Do not breastfeed. (8.2)

FULL PRESCRIBING INFORMATION

1 INDICATIONS AND USAGE

1.1 Adjuvant Treatment of Resected ALK-Positive Non-Small Cell Lung Cancer (NSCLC)

ALECENSA is indicated as adjuvant treatment in adult patients following tumor resection of anaplastic lymphoma kinase (ALK)-positive non-small cell lung cancer (NSCLC) (tumors ≥ 4 cm or node positive), as detected by an FDA-approved test [see Dosage & Administration (2.1)].

1.2 Treatment of Metastatic ALK-Positive NSCLC

ALECENSA is indicated for the treatment of adult patients with ALK-positive metastatic NSCLC as detected by an FDA-approved test [see Dosage & Administration (2.1)].

2 DOSAGE AND ADMINISTRATION

2.1 Patient Selection

Select patients with resectable tumors for the adjuvant treatment of NSCLC with ALECENSA based on the presence of ALK positivity in tumor tissue [see Indications and Usage (1.1) and Clinical Studies (14.1)].

Select patients for the treatment of metastatic NSCLC with ALECENSA based on the presence of ALK positivity in tumor tissue or plasma specimens [see Indications and Usage (1.2) and Clinical Studies (14.2)]. If ALK rearrangements are not detected in a plasma specimen, test tumor tissue if feasible.

Information on FDA-approved tests for the detection of ALK rearrangements in NSCLC is available at http://www.fda.gov/CompanionDiagnostics.

2.2 Dosing and Administration

The recommended dosage information for ALECENSA is provided in Table 1.

Table 1: ALECENSA Recommended Dosage and Duration of Treatment
Indication | Recommended Dosage of ALECENSA | Duration
Adjuvant treatment of resected NSCLC | 600 mg orally twice daily with food [see Clinical Pharmacology (12.3)] | For a total of 2 years or until disease recurrence or unacceptable toxicity
Metastatic NSCLC | 600 mg orally twice daily with food [see Clinical Pharmacology (12.3)] | Until disease progression or unacceptable toxicity
- Swallow capsules whole, do not open or dissolve the contents of the capsule.
- If a dose of ALECENSA is missed or vomiting occurs after taking a dose of ALECENSA, take the next dose at the scheduled time.

2.3 Recommended Dosage for Hepatic Impairment

The recommended dose of ALECENSA in patients with severe hepatic impairment (Child-Pugh C) is 450 mg orally twice daily [see Use in Specific Populations (8.7) and Clinical Pharmacology (12.3)].

2.4 Dose Modifications for Adverse Reactions

The dose reduction schedule for ALECENSA is provided in Table 2.

Table 2: ALECENSA Dose Reduction Schedule
Dose Reduction Schedule | Dose Level
Starting dose | 600 mg taken orally twice daily
First dose reduction | 450 mg taken orally twice daily
Second dose reduction | 300 mg taken orally twice daily

Discontinue if patients are unable to tolerate the 300 mg twice daily dose.

Recommendations for dose modifications of ALECENSA in case of adverse reactions are provided in Table 3.

Table 3: ALECENSA Dose Modifications for Adverse Reactions
Criteria [ALT = alanine transaminase; AST = aspartate transaminase; ULN = upper limit of normal; ILD = interstitial lung disease; CPK = blood creatine phosphokinase] | ALECENSA Dose Modification
ALT or AST elevation of greater than 5 times upper limit of normal (ULN) with total bilirubin less than or equal to 2 times ULN | Temporarily withhold until recovery to baseline or to less than or equal to 3 times ULN, then resume at reduced dose as per Table 2.
ALT or AST elevation greater than 3 times ULN with total bilirubin elevation greater than 2 times ULN in the absence of cholestasis or hemolysis | Permanently discontinue ALECENSA.
Total bilirubin elevation of greater than 3 times ULN | Temporarily withhold until recovery to baseline or to less than or equal to 1.5 times ULN, then resume at reduced dose as per Table 2.
Any grade treatment-related interstitial lung disease (ILD)/pneumonitis | Permanently discontinue ALECENSA.
Grade 3 renal impairment | Temporarily withhold until serum creatinine recovers to less than or equal to 1.5 times ULN, then resume at reduced dose.
Grade 4 renal impairment | Permanently discontinue ALECENSA.
Symptomatic bradycardia | Withhold ALECENSA until recovery to asymptomatic bradycardia or to a heart rate of 60 bpm or above. If contributing concomitant medication is identified and discontinued, or its dose is adjusted, resume ALECENSA at previous dose upon recovery to asymptomatic bradycardia or to a heart rate of 60 bpm or above. If no contributing concomitant medication is identified, or if contributing concomitant medications are not discontinued or dose modified, resume ALECENSA at reduced dose (see Table 2) upon recovery to asymptomatic bradycardia or to a heart rate of 60 bpm or above.
Bradycardia [Heart rate less than 60 beats per minute (bpm)] (life-threatening consequences, urgent intervention indicated) | Permanently discontinue ALECENSA if no contributing concomitant medication is identified. If contributing concomitant medication is identified and discontinued, or its dose is adjusted, resume ALECENSA at reduced dose (see Table 2) upon recovery to asymptomatic bradycardia or to a heart rate of 60 bpm or above, with frequent monitoring as clinically indicated. Permanently discontinue ALECENSA in case of recurrence.
CPK elevation greater than 5 times ULN | Temporarily withhold until recovery to baseline or to less than or equal to 2.5 times ULN, then resume at same dose.
CPK elevation greater than 10 times ULN or second occurrence of CPK elevation of greater than 5 times ULN | Temporarily withhold until recovery to baseline or to less than or equal to 2.5 times ULN, then resume at reduced dose as per Table 2.
Hemolytic Anemia | Withhold ALECENSA if hemolytic anemia is suspected. Upon resolution, resume at reduced dose or permanently discontinue.

3 DOSAGE FORMS AND STRENGTHS

150 mg hard capsules, white, with "ALE" printed in black ink on the cap and "150 mg" printed in black ink on the body.

4 CONTRAINDICATIONS

None.

5 WARNINGS AND PRECAUTIONS

5.1 Hepatotoxicity

Severe hepatotoxicity, including drug-induced liver injury, occurred in patients treated with ALECENSA.

In the pooled safety population [see Adverse Reactions (6.1)] of patients who received ALECENSA, hepatotoxicity occurred in 41% of patients and the incidence of Grade ≥ 3 hepatotoxicity was 8%. In the ALINA study, hepatotoxicity occurred in 61% of patients treated with ALECENSA and the incidence of Grade ≥ 3 hepatotoxicity was 4.7%. The majority (72% of 136 patients) of elevated transaminases occurred during the first 3 months of treatment. Treatment discontinuation due to hepatotoxicity occurred in 3.6% of patients who received ALECENSA in the pooled safety population and 1.6% of patients treated in the ALINA study.

In the pooled safety population, concurrent elevations in ALT or AST greater than or equal to 3 times the ULN and total bilirubin greater than or equal to 2 times the ULN, with normal alkaline phosphatase, occurred in less than 1% of patients treated with ALECENSA. Three patients with Grades 3–4 AST/ALT elevations had drug-induced liver injury (documented by liver biopsy in two cases).

Monitor liver function tests including ALT, AST, and total bilirubin every 2 weeks during the first 3 months of treatment, then once a month and as clinically indicated, with more frequent testing in patients who develop transaminase and bilirubin elevations. Based on the severity of the adverse drug reaction, withhold ALECENSA and resume at a reduced dose or permanently discontinue ALECENSA as described in Table 3 [see Dosage and Administration (2.4)].

5.2 Interstitial Lung Disease (ILD)/Pneumonitis

ILD/pneumonitis occurred in patients treated with ALECENSA.

In the pooled safety population [see Adverse Reactions (6.1)], ILD/pneumonitis occurred in 1.3% of patients treated with ALECENSA with 0.4% of patients experiencing Grade 3 ILD/pneumonitis.

Five patients (0.9%) in the pooled safety population discontinued ALECENSA due to ILD/pneumonitis. The median time-to-onset of Grade 3 or higher ILD/pneumonitis was 2.1 months (range: 0.6 months to 3.6 months).

Promptly investigate for ILD/pneumonitis in any patient who presents with worsening of respiratory symptoms indicative of ILD/pneumonitis (e.g., dyspnea, cough, and fever). Immediately withhold ALECENSA treatment in patients diagnosed with ILD/pneumonitis and permanently discontinue ALECENSA if no other potential causes of ILD/pneumonitis have been identified [see Dosage and Administration (2.4) and Adverse Reactions (6)].

5.3 Renal Impairment

Renal impairment, including fatal cases, occurred in patients treated with ALECENSA.

In the pooled safety population [see Adverse Reactions (6.1)], renal impairment occurred in 12% of patients treated with ALECENSA, including Grade ≥ 3 in 1.7% of patients, of which 0.4% were fatal events. The median time to Grade ≥ 3 renal impairment was 3.7 months (range 0.5 to 31.8 months). Dosage modifications for renal impairment were required in 2.4% of patients.

Permanently discontinue ALECENSA for Grade 4 renal toxicity. Withhold ALECENSA for Grade 3 renal toxicity until recovery to less than or equal to 1.5 times ULN, then resume at reduced dose [see Dosage and Administration (2.4)].

5.4 Bradycardia

Symptomatic bradycardia occurred in patients treated with ALECENSA.

In the pooled safety population [see Adverse Reactions (6.1)], bradycardia occurred in 11% of patients treated with ALECENSA. Twenty percent of 521 patients treated with ALECENSA, for whom serial electrocardiograms (ECGs) were available, had post-dose heart rates of less than 50 beats per minute (bpm).

Monitor heart rate and blood pressure regularly. For asymptomatic bradycardia dose modification is not required. For symptomatic bradycardia that is not life-threatening, withhold ALECENSA until recovery to asymptomatic bradycardia or to a heart rate ≥ 60 bpm and evaluate concomitant medications known to cause bradycardia, as well as anti-hypertensive medications. If bradycardia is attributable to a concomitant medication, resume ALECENSA at a reduced dose (see Table 2) upon recovery to asymptomatic bradycardia or to a heart rate of ≥ 60 bpm, with frequent monitoring as clinically indicated.

Permanently discontinue ALECENSA in cases of life-threatening bradycardia if no contributing concomitant medication is identified [see Dosage and Administration (2.4)]. Permanently discontinue ALECENSA for recurrence of life-threatening bradycardia.

5.5 Severe Myalgia and Creatine Phosphokinase (CPK) Elevation

Severe myalgia and creatine phosphokinase (CPK) elevation occurred in patients treated with ALECENSA.

In the pooled safety population [see Adverse Reactions (6.1)], myalgia (including muscle- and musculoskeletal-related reactions) occurred in 31% of patients treated with ALECENSA, including Grade ≥ 3 in 0.8% of patients. Dosage modifications for myalgia events were required in 2.1% of patients.

In the pooled safety population, of the 491 patients with CPK laboratory data available, elevated CPK occurred in 56% of patients treated with ALECENSA, including 6% Grade ≥ 3. The median time to Grade ≥ 3 CPK elevation was 15 days (interquartile range - 15 –337 days). Dosage modifications for elevation of CPK occurred in 5% of patients.

In the ALINA study, elevated CPK occurred in 77% of 128 patients with CPK laboratory data, including 6% Grade ≥ 3 elevations.

Advise patients to report any unexplained muscle pain, tenderness, or weakness. Assess CPK levels every 2 weeks for the first month of treatment and as clinically indicated in patients reporting symptoms. Based on the severity of the CPK elevation, withhold ALECENSA, then resume or reduce dose [see Dosage and Administration (2.4)].

5.6 Hemolytic Anemia

Hemolytic anemia occurred in patients treated with ALECENSA.

Hemolytic anemia was initially reported with ALECENSA in the postmarketing setting, including cases associated with a negative direct antiglobulin test (DAT) result. Assessments for the determination of hemolytic anemia were subsequently collected in the ALINA study, where hemolytic anemia was observed in 3.1% of patients treated with ALECENSA. If hemolytic anemia is suspected, withhold ALECENSA and initiate appropriate laboratory testing. If hemolytic anemia is confirmed, consider resuming at a reduced dose upon resolution or permanently discontinue ALECENSA [see Dosage and Administration (2.4)].

5.7 Embryo-Fetal Toxicity

Based on findings from animal studies and its mechanism of action, ALECENSA can cause fetal harm when administered to pregnant women. Oral administration of alectinib to pregnant rats and rabbits during the period of organogenesis resulted in embryo-fetal toxicity and abortion at maternally toxic doses with exposures approximately 2.7-fold those observed in humans with alectinib 600 mg twice daily. Advise pregnant women and females of reproductive potential of the potential risk to a fetus.

Advise females of reproductive potential to use effective contraception during treatment with ALECENSA and for 5 weeks following the last dose [see Use in Specific Populations (8.1 and 8.3) and Clinical Pharmacology (12.1)].

6 ADVERSE REACTIONS

The following adverse reactions are discussed in greater detail in other sections of the label:

- Hepatotoxicity [see Warnings and Precautions (5.1)]
- Interstitial Lung Disease (ILD)/Pneumonitis [see Warnings and Precautions (5.2)]
- Renal Impairment [see Warnings and Precautions (5.3)]
- Bradycardia [see Warnings and Precautions (5.4)]
- Severe Myalgia and Creatine Phosphokinase (CPK) Elevation [see Warnings and Precautions (5.5)]
- Hemolytic Anemia [see Warnings and Precautions (5.6)]
- Embryo-Fetal Toxicity [see Warnings and Precautions (5.7)]

6.1 Clinical Trials Experience

Because clinical trials are conducted under widely varying conditions, adverse reaction rates observed in the clinical trials of a drug cannot be directly compared to rates in the clinical trials of another drug and may not reflect the rates observed in practice.

The pooled safety population described in the WARNINGS AND PRECAUTIONS reflect exposure to ALECENSA as a single agent at 600 mg orally twice daily in 533 patients in Studies NP28761, NP28673, ALEX and ALINA [see Clinical Studies (14)]. Among 533 patients who received ALECENSA, 75% were exposed for 6 months or longer and 64% were exposed for greater than one year. In this pooled safety population, the most common (≥ 20%) adverse reactions were hepatotoxicity (41%), constipation (39%), fatigue (36%), myalgia (31%), edema (29%), rash (23%) and cough (21%). The most common (≥ 2%) Grade 3 or 4 laboratory abnormalities were increased CPK (6%), decreased hemoglobin (4.4%), increased ALT (4.2%), increased bilirubin (4.0%) and increased AST (3.4%).

Adjuvant Treatment of Resected ALK-Positive NSCLC

The safety of ALECENSA was evaluated in ALINA, a multi-center, open-label, randomized trial for the adjuvant treatment of patients with resected ALK-positive NSCLC [see Clinical Studies (14.1)]. At the time of DFS analysis, the median duration of exposure was 23.9 months for ALECENSA and 2.1 months for platinum-based chemotherapy.

Serious adverse reactions occurred in 13% of patients treated with ALECENSA; the most frequent serious adverse reactions (≥ 1%) were pneumonia (3.9%), appendicitis (3.1%), and acute myocardial infarction (1.6%). Permanent discontinuation of ALECENSA due to an adverse event occurred in 5% of patients; the most frequent adverse reactions (≥ 1%) that led to treatment discontinuation were pneumonitis and hepatotoxicity.

Dosage interruptions of ALECENSA due to an adverse reaction occurred in 27% of patients. Adverse reactions which required dosage interruption in ≥ 2% of patients included hepatotoxicity, increased blood CPK, COVID-19, myalgia, abdominal pain, and pneumonia.

Dose reductions of ALECENSA due to an adverse reaction occurred in 26% of patients. Adverse reactions which required dose reductions in ≥ 2% of patients included hepatotoxicity, increased blood CPK, rash, bradycardia and myalgia.

Table 4 and 5 summarize the common adverse reactions and laboratory abnormalities observed in ALINA.

Table 4: Adverse Reactions (≥ 10%) in Patients Treated with ALECENSA in ALINA
Adverse Reaction | ALECENSA N=128 |  | Chemotherapy N=120
Adverse Reaction | All Grades (%) | Grades 3-4 (%) | All Grades (%) | Grades 3-4 (%)
Adverse Reaction | Hepatobiliary System Disorders
Hepatotoxicity [Includes increased alanine aminotransferase, increased aspartate aminotransferase, increased bile acids, increased conjugated bilirubin, increased blood bilirubin, increased unconjugated blood bilirubin, increased gamma-glutamyltransferase, hepatotoxicity, hyperbilirubinemia, increased liver function test, ocular icterus and increased transaminases.] | 61 | 4.7 [All events are Grade 3] | 13 | 0
Gastrointestinal Disorders
Constipation | 42 | 0.8 | 25 | 0.8
Abdominal pain [Includes abdominal discomfort, abdominal pain, lower abdominal pain, upper abdominal pain, abdominal tenderness, epigastric discomfort and gastrointestinal pain.] | 13 | 0 | 10 | 1.7
Diarrhea [Includes colitis and diarrhea.] | 13 | 0.8 | 9 | 1.7
Musculoskeletal
Myalgia [Includes muscle fatigue, muscular weakness, musculoskeletal chest pain, musculoskeletal stiffness and myalgia.] | 34 | 0.8 | 1.7 | 0
Infections and Infestations
COVID-19 | 29 | 0 | 0.8 | 0
General Disorders and Administration Site Conditions
Fatigue [Includes asthenia and fatigue.] | 25 | 0.8 | 28 | 4.2
Edema [Includes edema, face edema, localized edema, peripheral edema, face swelling and peripheral swelling.] | 16 | 0 | 1.7 | 0
Skin and Subcutaneous Tissue Disorders
Rash [Includes acneiform dermatitis, bullous dermatitis, drug eruption, eczema, rash, erythematous rash, maculo-papular rash, papular rash, seborrheic dermatitis, urticaria and xeroderma.] | 23 | 1.6 | 10 | 0
Respiratory System Disorders
Cough [Includes cough and productive cough.] | 20 | 0.8 | 3.3 | 0
Dyspnea [Includes dyspnea and exertional dyspnea.] | 13 | 0.8 | 2.5 | 0
Renal
Renal Impairment [Includes azotemia, increased blood creatinine, decreased renal creatinine clearance, decreased glomerular filtration rate, hypercreatininemia, renal impairment and renal failure.] | 16 | 0.8 | 9 | 0
Nervous System Disorders
Dysgeusia [Includes dysgeusia and taste disorder.] | 13 | 0 | 3.3 | 0
Headache | 11 | 0 | 7 | 0
Investigations
Increased weight | 13 | 0.8 | 0.8 | 0
Cardiac Disorders
Bradycardia [Includes bradycardia and sinus bradycardia.] | 12 | 0 | 0 | 0
Based on NCI CTCAE v5.0

Clinically significant adverse reactions in < 10% of patients who received ALECENSA in ALINA: nausea (8%), vomiting (7%), vision disorders (4.7%; includes blurred vision, visual acuity reduced and photopsia), stomatitis (4.7%; includes stomatitis and mouth ulceration), photosensitivity reaction (3.9%) and pneumonitis (2.3%).

Table 5: Worsening in Laboratory Values from Baseline Occurring in ≥ 20% of Patients in Treated with ALECENSA in ALINA
Parameter | ALECENSA N=128 |  | Chemotherapy N=120
Parameter | All Grades (%) | Grades 3–4 (%) | All Grades (%) | Grades 3–4 (%)
Parameter | Chemistry
Increased CPK | 77 | 8 | 8 | 1.7 [All events were Grade 3]
Increased AST | 75 | 0.8 | 25 | 0
Increased bilirubin | 68 | 2.3 | 4.2 | 0
Increased alkaline phosphatase | 64 | 0 | 14 | 0
Increased ALT | 57 | 2.3 | 28 | 0
Increased creatinine | 41 | 0 | 23 | 0
Increased uric acid | 30 | 0 | 19 | 0
Hematology
Decreased hemoglobin | 69 | 0 | 67 | 0.8
Based on NCI CTCAE v5.0

Previously Untreated Metastatic ALK-Positive NSCLC

The safety of ALECENSA was evaluated in 152 patients with ALK-positive NSCLC in the ALEX study. The median duration of exposure to ALECENSA was 17.9 months. Patient characteristics of the ALEX study population (n=303) were: median age 56 years, age less than 65 (77%), female (56%), Caucasian (50%), Asian (46%), adenocarcinoma histology (92%), never smoker (63%), and ECOG PS 0 or 1 (93%).

Serious adverse reactions occurred in 28% of patients treated with ALECENSA; serious adverse reactions reported in 2% or more of patients treated with ALECENSA were pneumonia (4.6%), and renal impairment (3.9%). Grade ≥ 3 adverse events were reported for 41% of patients in the ALECENSA arm. Fatal adverse reactions occurred in 3.3% of patients treated with ALECENSA; these were renal impairment (2 patients), sudden death, cardiac arrest, and pneumonia (1 patient each). Permanent discontinuation of ALECENSA for adverse reactions occurred in 11% of patients. Adverse drug reactions that led to discontinuation of ALECENSA in 1% or more of patients were renal impairment (2.0%), hyperbilirubinemia (1.3%), increased ALT (1.3%), and increased AST (1.3%). Dosage interruptions of ALECENSA due to an adverse reaction occurred in 20% of patients. Adverse reactions which required dosage interruption in > 2% of patients included increased ALT, pneumonia. Dose reductions of ALECENSA due to an adverse reaction occurred in 17% of patients. Adverse reactions which required dose reductions in > 2% of patients included hyperbilirubinemia, increased AST and increased ALT.

Tables 6 and 7 summarize the common adverse reactions and laboratory abnormalities observed in ALEX.

Table 6: Adverse Drug Reactions (>10% for all NCI CTCAE Grades or ≥2% for Grades 3-4) in Patients Treated with ALECENSA in ALEX
Adverse Reaction | ALECENSA N=152 |  | Crizotinib N=151
Adverse Reaction | All Grades (%) | Grades 3-4 (%) | All Grades (%) | Grades 3-4 (%)
Adverse Reaction | Gastrointestinal
Constipation | 34 | 0 | 33 | 0
Nausea | 14 | 0.7 | 48 | 3.3
Diarrhea | 12 | 0 | 45 | 2.0
General
Fatigue [Includes fatigue and asthenia.] | 26 | 1.3 | 23 | 0.7
Edema [Includes peripheral edema, edema, eyelid edema, localized edema, and face edema.] | 22 | 0.7 | 34 | 0.7
Musculoskeletal
Myalgia [Includes myalgia and musculoskeletal pain.] | 23 | 0 | 4.0 | 0
Skin
Rash [Includes rash, rash maculo-papular, dermatitis acneiform, erythema, generalized rash, rash macular, rash papular, exfoliative rash, and pruritic rash.] | 15 | 0.7 | 13 | 0
Cardiac
Bradycardia [Includes reported cases of bradycardia and sinus bradycardia but is not based on serial ECG assessment.] | 11 | 0 | 15 | 0
Renal
Renal impairment [Includes increased blood creatinine, creatinine renal clearance decreased, glomerular filtration rate decreased, and acute kidney injury.] | 12 | 3.9 [Includes two Grade 5 events.] | 0 | 0
NCI CTCAE = National Cancer Institute Common Terminology Criteria for Adverse Events; MedDRA = Medical Dictionary for Regulatory Activities; SOC = System Organ Class.

The following additional clinically significant adverse drug reactions were observed in patients treated with ALECENSA: weight gain (9.9%), vomiting (7%), photosensitivity reaction (5.3%), vision disorders (4.6%; includes blurred vision, visual impairment, vitreous floaters reduced visual acuity and diplopia), stomatitis (3.3%), dysgeusia (3.3%; includes hypogeusia), interstitial lung disease (1.3%), and drug-induced liver injury (1.3%).

Table 7: Worsening in Laboratory Values Occurring in > 10% of Patients in ALEX
Parameter | ALECENSA N=152 |  | Crizotinib N=151
 | All Grades (%) | Grades 3–4 (%) | All Grades (%) | Grades 3–4 (%)
Chemistry
Hyperbilirubinemia [n=147 for alectinib (with baseline values missing for 1 of these patients), n=148 for crizotinib.] | 54 | 5 | 4.7 | 0
Increased AST [n=147 for alectinib (with baseline values missing for 2 of these patients), n=148 for crizotinib.] | 50 | 6 | 56 | 11
Increased alkaline phosphatase [n=147 for alectinib, n=148 for crizotinib.] | 50 | 0 | 44 | 0
Increased ALT | 40 | 6 | 62 | 16
Increased creatinine, [Only patients with creatinine increases based on ULN definition.] | 38 | 4.1 | 23 | 0.7
Increased CPK [n=143 for alectinib (with baseline values missing for 14 of these patients), n=143 for crizotinib (with baseline values missing for 13 of these patients).] | 37 | 2.8 | 52 | 1.4
Hypocalcemia | 29 | 0 | 61 | 1.4
Hyperglycemia [n=134 for alectinib (with baseline values missing for 18 of these patients), n=131 for crizotinib (with baseline values missing for 8 of these patients).] | 22 | 2.2 | 19 | 2.3
Hyponatremia [n=147 for alectinib, n=148 for crizotinib (with baseline values missing for 1 of these patients).] | 18 | 6 | 20 | 4.1
Hypokalemia | 17 | 2 | 12 | 0.7
Hypoalbuminemia [n=146 for alectinib (with baseline values missing for 1 of these patients), n=148 for crizotinib (with baseline values missing for 1 of these patients).] | 14 | 0 | 57 | 3.4
Hyperkalemia | 12 | 1.4 | 16 | 1.4
Hypophosphatemia [n=145 for alectinib (with baseline values missing for 2 of these patients), n=148 for crizotinib (with baseline values missing for 4 of these patients).] | 9 | 1.4 | 25 | 2.7
Increased gamma glutamyl transferase [n=143 for alectinib (with baseline values missing for 4 of these patients), n=148 (with baseline values missing for 5 of these patients).] | 7 | 0.7 | 39 | 4.1
Hematology
Anemia | 62 | 7 | 36 | 0.7
Lymphopenia | 14 | 1.4 | 34 | 4.1
Neutropenia | 14 | 0 | 36 | 7
Note: Based on National Cancer Institute Common Terminology Criteria for Adverse Events v4.03.
Excludes patients with no post-baseline lab assessments.

Metastatic ALK-Positive NSCLC Previously Treated with Crizotinib

The safety of ALECENSA was evaluated in 253 patients with ALK-positive non-small cell lung cancer (NSCLC) treated with ALECENSA in two clinical trials, Studies NP28761 and NP28673. The median duration of exposure to ALECENSA was 9.3 months. One hundred sixty-nine patients (67%) were exposed to ALECENSA for more than 6 months, and 100 patients (40%) for more than one year. The population characteristics were: median age 53 years, age less than 65 (86%), female (55%), White (74%), Asian (18%), NSCLC adenocarcinoma histology (96%), never or former smoker (98%), ECOG Performance Status (PS) 0 or 1 (91%), and prior chemotherapy treatment (78%).

Serious adverse reactions occurred in 19% of patients; the most frequently reported serious adverse reactions were pulmonary embolism (1.2%), dyspnea (1.2%), and hyperbilirubinemia (1.2%). Fatal adverse reactions occurred in 2.8% of patients and included hemorrhage (0.8%), intestinal perforation (0.4%), dyspnea (0.4%), pulmonary embolism (0.4%), and endocarditis (0.4%). Permanent discontinuation of ALECENSA for adverse reactions occurred in 6% of patients. The most frequent adverse reactions that led to permanent discontinuation were hyperbilirubinemia (1.6%), increased ALT levels (1.6%), and increased AST levels (1.2%). Overall, 23% of patients initiating treatment at the recommended dose required at least one dose reduction. The median time to first dose reduction was 48 days. The most frequent adverse reactions that led to dose reductions or interruptions were elevations in bilirubin (6%), CPK (4.3%), ALT (4.0%), AST (2.8%), and vomiting (2.8%).

Tables 8 and 9 summarize the common adverse reactions and laboratory abnormalities observed in Studies NP28761 and NP28673.

Table 8: Adverse Reactions in ≥ 10% (All Grades) or ≥ 2% (Grades 3–4) of Patients in Studies NP28761 and NP28673
Adverse Reactions | ALECENSA N=253
Adverse Reactions | All Grades (%) | Grades 3–4 (%) [Per Common Terminology Criteria for Adverse Events (CTCAE) version 4.0]
Fatigue [Includes fatigue and asthenia.] | 41 | 1.2
Constipation | 34 | 0
Edema [Includes peripheral edema, edema, generalized edema, eyelid edema, and periorbital edema.] | 30 | 0.8
Myalgia [Includes myalgia and musculoskeletal pain.] | 29 | 1.2
Cough | 19 | 0
Rash [Includes rash, maculopapular rash, acneiform dermatitis, erythema, generalized rash, papular rash, pruritic rash, and macular rash.] | 18 | 0.4
Nausea | 18 | 0
Headache | 17 | 0.8
Diarrhea | 16 | 1.2
Dyspnea | 16 | 3.6 [Includes one Grade 5 event.]
Back pain | 12 | 0
Vomiting | 12 | 0.4
Increased weight | 11 | 0.4
Vision disorder [Includes blurred vision, vitreous floaters, visual impairment, reduced visual acuity, asthenopia, and diplopia.] | 10 | 0

An additional clinically significant adverse drug reaction was photosensitivity, which occurred in 9.9% of patients exposed to ALECENSA in Studies NP28761 and NP28673. Patients were advised to avoid sun exposure and to use broad-spectrum sunscreen. The incidence of Grade 2 photosensitivity was 0.4%; the remaining events were Grade 1 in severity.

Table 9: Treatment-Emergent Worsening in Laboratory Values Occurring in > 20% of Patients in Studies NP28761 and NP28673
Parameter | ALECENSA N=250
Parameter | All Grades (%) | Grades 3–4 (%) [Per CTCAE version 4.0]
Chemistry
Increased AST | 51 | 3.6
Increased Alkaline Phosphatase | 47 | 1.2
Increased CPK [n=218 for CPK (with baseline values missing for 91 of these patients).] | 43 | 4.6
Hyperbilirubinemia | 39 | 2.4
Hyperglycemia [n=152 for fasting blood glucose (with baseline values missing for 5 of these patients).] | 36 | 2.0
Increased ALT | 34 | 4.8
Hypocalcemia | 32 | 0.4
Hypokalemia | 29 | 4.0
Increased Creatinine [Only patients with creatinine increases based on ULN definition.] | 28 | 0
Hypophosphatemia | 21 | 2.8
Hyponatremia | 20 | 2.0
Hematology
Anemia | 56 | 2.0
Lymphopenia [n=217 for lymphocytes (with baseline values missing for 5 of these patients).] | 22 | 4.6

8 USE IN SPECIFIC POPULATIONS

8.1 Pregnancy

Risk Summary

Based on findings from animal studies and its mechanism of action, ALECENSA can cause fetal harm when administered to a pregnant woman [see Clinical Pharmacology (12.1)]. There are no available data on ALECENSA use in pregnant women.

Administration of alectinib to pregnant rats and rabbits by oral gavage during the period of organogenesis resulted in embryo-fetal toxicity and abortion at maternally toxic doses with exposures approximately 2.7-fold those observed in humans treated with alectinib at 600 mg twice daily (see Data). Advise pregnant women of the potential risk to a fetus.

In the U.S. general population, the estimated background risk of major birth defects and miscarriage in clinically recognized pregnancies is 2% to 4% and 15% to 20%, respectively.

Data

Animal Data

In a preliminary rabbit embryo-fetal study, administration of alectinib by oral gavage during the period of organogenesis resulted in abortion or complete embryo-fetal mortality at a maternally toxic dose of 27 mg/kg/day (approximately 2.9-fold the estimated area under the curve (AUC0-24h,ss) in humans treated with alectinib 600 mg twice daily) in three of six pregnant rabbits. The remaining three pregnant rabbits in this group had few live fetuses, decreased fetal and placental weights, and retroesophageal subclavian artery. In a rat preliminary embryo-fetal development study, administration of alectinib during organogenesis resulted in complete litter loss in all pregnant rats at 27 mg/kg/day (approximately 4.5-fold the estimated AUC0-24h,ss in humans treated with alectinib 600 mg twice daily). Doses greater than or equal to 9 mg/kg/day (approximately 2.7-fold the estimated human AUC0-24h,ss in humans treated with alectinib 600 mg twice daily), resulted in maternal toxicity as well as developmental toxicities including decreased fetal weight, dilated ureter, thymic cord, small ventricle and thin ventricle wall, and reduced number of sacral and caudal vertebrae.

8.2 Lactation

Risk Summary

There are no data on the presence of alectinib or its metabolites in human milk, the effects of alectinib on the breastfed child, or its effects on milk production. Because of the potential for serious adverse reactions in breastfed children from alectinib, advise a lactating woman not to breastfeed during treatment with ALECENSA and for 1 week after the last dose.

8.3 Females and Males of Reproductive Potential

ALECENSA can cause fetal harm when administered to a pregnant woman [see Use in Specific Populations (8.1)].

Pregnancy Testing

Verify pregnancy status in females of reproductive potential prior to initiating ALECENSA [see Use in Specific Populations (8.1)].

Contraception

Females

Advise females of reproductive potential to use effective contraception during treatment with ALECENSA and for 5 weeks after the last dose [see Use in Specific Populations (8.1)].

Males

Based on genotoxicity findings, advise males with female partners of reproductive potential to use effective contraception during treatment with ALECENSA and for 3 months following the last dose [see Nonclinical Toxicology (13.1)].

8.4 Pediatric Use

The safety and effectiveness of ALECENSA in pediatric patients have not been established.

Animal Data

Juvenile animal studies have not been conducted using alectinib. In general toxicology studies, treatment of rats with doses of alectinib resulting in exposures greater than or equal to approximately 4.5-fold those in humans treated with alectinib at 600 mg twice daily resulted in changes in the growing teeth and bones. Findings in teeth included discoloration and changes in tooth size along with histopathological disarrangement of the ameloblast and odontoblast layers. There were also decreases in the trabecular bone and increased osteoclast activity in the femur and sternum.

8.5 Geriatric Use

Nineteen percent of the 533 patients studied in NP28761, NP28673, ALEX and ALINA were 65 years of age and older (3.2% were 75 years of age and older). No overall differences in effectiveness were observed based on age. Exploratory analysis suggests a higher incidence of serious adverse events (38% vs 25%), more frequent adverse events leading to treatment discontinuations (18% vs 6%) and dose modifications (48% vs 35%) in patients 65 years or older as compared to those younger than 65 years.

8.6 Renal Impairment

No dose adjustment is recommended for patients with mild or moderate renal impairment. The safety of ALECENSA in patients with severe renal impairment (creatinine clearance less than 30 mL/min) or end-stage renal disease has not been studied [see Clinical Pharmacology (12.3)].

8.7 Hepatic Impairment

No dose adjustment is recommended for patients with mild (Child-Pugh A) or moderate (Child-Pugh B) hepatic impairment. Increased exposure of alectinib occurred in patients with severe hepatic impairment (Child-Pugh C). The recommended dose of ALECENSA in patients with severe hepatic impairment (Child-Pugh C) is 450 mg orally twice daily [see Dosage and Administration (2.3) and Clinical Pharmacology (12.3)].

10 OVERDOSAGE

No experience with overdose is available. There is no specific antidote for overdose with ALECENSA. Alectinib and its major active metabolite M4 are > 99% bound to plasma proteins; therefore, hemodialysis is likely to be ineffective in the treatment of overdose.

11 DESCRIPTION

ALECENSA (alectinib) is a kinase inhibitor for oral administration. The molecular formula for alectinib is C30H34N4O2 ∙ HCl. The molecular weight is 482.62 g/mol (free base form) and 519.08 g/mol (hydrochloride salt). Alectinib is described chemically as 9-ethyl-6, 6-dimethyl-8-[4-(morpholin-4-yl)piperidin-1-yl]-11-oxo-6, 11-dihydro-5H-benzo[b]carbazole-3-carbonitrile hydrochloride. The chemical structure of alectinib is shown below:

Alectinib HCl is a white to yellow white powder or powder with lumps with a pKa of 7.05 (base).

ALECENSA is supplied as hard capsules containing 150 mg of alectinib (equivalent to 161.33 mg alectinib HCl) and the following inactive ingredients: lactose monohydrate, hydroxypropylcellulose, sodium lauryl sulfate, magnesium stearate, and carboxymethylcellulose calcium. The capsule shell contains hypromellose, carrageenan, potassium chloride, titanium dioxide, corn starch, and carnauba wax. The printing ink contains red iron oxide (E172), yellow iron oxide (E172), FD&C Blue No. 2 aluminum lake (E132), carnauba wax, white shellac, and glyceryl monooleate.

12 CLINICAL PHARMACOLOGY

12.1 Mechanism of Action

Alectinib is a tyrosine kinase inhibitor that targets ALK and RET. In nonclinical studies, alectinib inhibited ALK phosphorylation and ALK-mediated activation of the downstream signaling proteins STAT3 and AKT, and decreased tumor cell viability in multiple cell lines harboring ALK fusions, amplifications, or activating mutations. The major active metabolite of alectinib, M4, showed similar in vitro potency and activity.

Alectinib and M4 demonstrated in vitro and in vivo activity against multiple mutant forms of the ALK enzyme, including some mutations identified in NSCLC tumors in patients who have progressed on crizotinib.

In mouse models implanted with tumors carrying ALK fusions, administration of alectinib resulted in antitumor activity and prolonged survival, including in mouse models implanted intracranially with ALK-driven tumor cell lines.

12.2 Pharmacodynamics

Cardiac Electrophysiology

The ability of alectinib to prolong the QT interval was assessed in 221 patients administered ALECENSA 600 mg twice daily in clinical studies. ALECENSA did not prolong the QTc (QT corrected for heart rate) interval to any clinically relevant extent. One patient had a maximum post-baseline QTcF value of greater than 500 msec, and one patient had a maximum QTcF change from baseline of greater than 60 msec.

12.3 Pharmacokinetics

The pharmacokinetics of alectinib and its major active metabolite M4 have been characterized in patients with ALK-positive NSCLC and healthy subjects.

In patients with ALK-positive NSCLC, the geometric mean (coefficient of variation %) steady-state maximal concentration (Cmax,ss) for alectinib was 665 ng/mL (44%) and for M4 was 246 ng/mL (45%) with peak to trough concentration ratio of 1.2. The geometric mean steady-state area under the curve from 0 to 12 hours (AUC0-12h,ss) for alectinib was 7,430 ng*h/mL (46%) and for M4 was 2,810 ng*h/mL (46%). Alectinib exposure is dose proportional across the dose range of 460 mg to 900 mg (i.e., 0.75 to 1.5 times the approved recommended dosage) under fed conditions. Alectinib and M4 reached steady-state concentrations by day 7. The geometric mean accumulation was approximately 6-fold for both alectinib and M4.

Absorption

Alectinib reached maximal concentrations at 4 hours following administration of ALECENSA 600 mg twice daily under fed conditions in patients with ALK-positive NSCLC.

The absolute bioavailability of alectinib was 37% (90% CI: 34%, 40%) under fed conditions.

A high-fat, high-calorie meal increased the combined exposure (AUC0-inf) of alectinib plus M4 by 3.1-fold (90% CI: 2.7, 3.6) following oral administration of a single 600 mg dose of ALECENSA.

Distribution

The apparent volume of distribution is 4,016 L for alectinib and 10,093 L for M4.

Alectinib and M4 are bound to human plasma proteins greater than 99%, independent of drug concentration.

Alectinib concentrations in the cerebrospinal fluid in patients with ALK-positive NSCLC approximate estimated alectinib free concentrations in the plasma.

In vitro studies suggest that alectinib is not a substrate of P-glycoprotein (P-gp), but M4 is a substrate of P-gp. Alectinib and M4 are not substrates of breast cancer resistance protein (BCRP), organic anion-transporting polypeptide (OATP) 1B1, or OATP1B3.

Elimination

The apparent clearance (CL/F) is 81.9 L/hour for alectinib and 217 L/hour for M4. The geometric mean elimination half-life is 33 hours for alectinib and 31 hours for M4 in patients with ALK-positive NSCLC.

Metabolism

Alectinib is metabolized by CYP3A4 to its major active metabolite M4. The geometric mean metabolite/parent exposure ratio at steady-state is 0.40. M4 is subsequently metabolized by CYP3A4. Alectinib and M4 were the main circulating moieties in plasma, constituting 76% of the total radioactivity.

Excretion

Ninety-eight percent of the radioactivity was excreted in feces following oral administration of a single radiolabeled dose of alectinib under fed conditions. Eighty-four percent of the dose was excreted in the feces as unchanged alectinib, and 6% of the dose was excreted as M4. Excretion of radioactivity in urine was less than 0.5% of administered radiolabeled dose of alectinib.

Specific Populations

Age (21 to 83 years), body weight (38 to 128 kg), mild hepatic impairment (total bilirubin ≤ ULN and AST > ULN or total bilirubin 1 to ≤ 1.5 × ULN and AST any value), mild to moderate renal impairment (creatinine clearance 30 to 89 mL/min), race (White, Asian, and Other), and sex had no clinically meaningful effect on the systemic exposure of alectinib and M4. The pharmacokinetics of alectinib have not been studied in patients with severe renal impairment (creatinine clearance < 30 mL/min), or end-stage renal disease.

Hepatic Impairment: Following administration of a single oral dose of 300 mg ALECENSA, the geometric mean ratio [90% confidence interval] for the combined AUCinf of alectinib and M4 in subjects with moderate hepatic impairment (Child-Pugh B) was 1.36 [0.947, 1.96] and in subjects with severe hepatic impairment (Child-Pugh C) was 1.76 [0.984, 3.15] as compared to that in subjects with normal hepatic function. The combined Cmax of alectinib and M4 was comparable among the three groups. No dose adjustment is recommended for patients with mild or moderate hepatic impairment. The recommended dose of ALECENSA in patients with severe hepatic impairment is 450 mg orally twice daily [see Dosage and Administration (2.3) and Use in Specific Populations (8.7)].

Drug Interactions

Effect of Other Drugs on Alectinib

No clinically meaningful effect on the combined exposure of alectinib plus M4 was observed in clinical studies following co-administration of ALECENSA with a strong CYP3A inhibitor (posaconazole), a strong CYP3A inducer (rifampin), or an acid-reducing agent (esomeprazole).

Effect of Alectinib on Other Drugs

No clinically meaningful effect on the exposure of midazolam (sensitive CYP3A substrate) or repaglinide (sensitive CYP2C8 substrate) is expected following co-administration with ALECENSA.

In vitro studies suggest that alectinib and M4 do not inhibit CYP1A2, 2B6, 2C9, 2C19 or 2D6.

In vitro studies suggest that alectinib and M4 inhibit P-gp and BCRP. Alectinib did not inhibit OATP1B1, OATP1B3, OAT1, OAT3, or OCT2 transport activity in vitro.

13 NONCLINICAL TOXICOLOGY

13.1 Carcinogenesis, Mutagenesis, Impairment of Fertility

Carcinogenicity studies with alectinib have not been conducted.

Alectinib was not mutagenic in vitro in the bacterial reverse mutation (Ames) assay, but was positive with an increased number of micronuclei in a rat bone marrow micronucleus test. The mechanism of micronucleus induction was abnormal chromosome segregation (aneugenicity) and not a clastogenic effect on chromosomes.

No studies in animals have been performed to evaluate the effect of alectinib on fertility. No adverse effects on male and female reproductive organs were observed in general toxicology studies conducted in rats and monkeys.

14 CLINICAL STUDIES

14.1 Adjuvant Treatment of Resected ALK-Positive NSCLC

The efficacy of ALECENSA for the adjuvant treatment of patients with ALK-positive NSCLC following complete tumor resection was evaluated in a global, randomized open-label clinical trial (ALINA: NCT03456076). Eligible patients were required to have resectable ALK-positive NSCLC, Stage IB (tumors ≥ 4 cm) – IIIA per the Union for International Cancer Control/American Joint Committee on Cancer (UICC/AJCC) Staging System, 7th Edition. ALK rearrangements were identified by a locally performed FDA-approved ALK test or by a centrally performed VENTANA ALK (D5F3) CDx assay.

Randomization was stratified by race (Asian vs. other races) and stage of disease (IB vs. II vs. IIIA). Patients were randomized (1:1) to receive ALECENSA 600 mg orally twice daily or platinum-based chemotherapy following tumor resection. Treatment with ALECENSA continued for a total of 2 years, or until disease recurrence or unacceptable toxicity. Platinum-based chemotherapy was administered intravenously for 4 cycles, with each cycle lasting 21 days, according to one of the following regimens:

- Cisplatin 75 mg/m^2 on Day 1 plus vinorelbine 25 mg/m^2 on Days 1 and 8
- Cisplatin 75 mg/m^2 on Day 1 plus gemcitabine 1250 mg/m^2 on Days 1 and 8
- Cisplatin 75 mg/m^2 on Day 1 plus pemetrexed 500 mg/m^2 on Day 1

In the event of intolerance to a cisplatin-based regimen, carboplatin was administered instead of cisplatin in the above combinations at a dose of AUC 5 mg/mL/min or 6 mg/mL/min.

The major efficacy outcome measures were disease-free survival (DFS) in patients with stage II-IIIA NSCLC and DFS in patients with stage IB-IIIA NSCLC (intent-to-treat [ITT] population) as assessed by investigator. DFS was defined as the time from date of randomization to the date of occurrence of any of the following: first documented recurrence of disease, new primary NSCLC, or death due to any cause, whichever occurred first. An additional efficacy outcome measure was overall survival (OS) in the ITT population.

A total of 257 patients were randomized to ALECENSA (N=130) or to chemotherapy (N=127). The median age was 56 years (range: 26 to 87), 24% were ≥ 65 years old; 52% were female; 56% were Asian, 42% were White, 0.4% were Black or African American, 2.3% were race unknown; 0.4% were Hispanic or Latino; 60% were never smokers; 53% had an ECOG PS of 0; 10% of patients had Stage IB, 35% had Stage II and 55% had Stage IIIA disease.

ALINA demonstrated a statistically significant improvement in DFS for patients treated with ALECENSA compared to patients treated with chemotherapy. OS data were not mature at the time of DFS analysis with 2.3% of deaths reported in the ITT population.

The efficacy results from ALINA are summarized in Table 10 and Figure 1.

Table 10: Investigator-Assessed DFS Results in ALINA
Efficacy Parameter | Stage II-IIIA Population |  | ITT Population
Efficacy Parameter | ALECENSA N=116 | Chemotherapy N=115 | ALECENSA N=130 | Chemotherapy N=127
Efficacy Parameter | DFS events (%) | 14 (12) | 45 (39) | 15 (12) | 50 (39)
Disease recurrence (%) | 14 (12) | 44 (38) | 15 (12) | 49 (38)
Death | 0 | 1 (0.9) | 0 | 1 (0.8)
Median DFS, months (95% CI) [Kaplan-Meier method.] | NR (NE, NE) | 44.4 (27.8, NE) | NR (NE, NE) | 41.3 (28.5, NE)
Hazard Ratio (95% CI) [Stratified Cox model, stratified by race (Asian vs. other races) in Stage II-IIIA and stratified by race (Asian vs. other races) and tumor stage (Stage IB vs. II vs. IIIA) in ITT.] | 0.24 (0.13, 0.45) |  | 0.24 (0.13, 0.43)
p-value [Stratified log-rank test stratified by race (Asian vs. other races) in Stage II-IIIA and stratified by race (Asian vs. other races) and tumor stage (Stage IB vs. II vs. IIIA) in ITT.] | <0.0001 |  | <0.0001
DFS = Disease-Free Survival; ITT = Intent-to-Treat; CI = Confidence Interval; NR = Not Reached; NE = Not Estimable.

Figure 1: Kaplan-Meier Curves of Investigator-Assessed DFS (ITT Population) in ALINA

In an exploratory analysis of site(s) of relapse, the proportion of patients with brain involvement at the time of disease recurrence was 4 patients (3.1%) in the ALECENSA arm and 14 patients (11%) in the chemotherapy arm.

14.2 Treatment of Metastatic ALK-Positive NSCLC

Previously Untreated Metastatic ALK-Positive NSCLC

The efficacy of ALECENSA for the treatment of patients with ALK-positive NSCLC who had not received prior systemic therapy for metastatic disease was established in an open-label, randomized, active-controlled, multicenter study (ALEX: NCT02075840). Patients were required to have an ECOG performance status of 0-2 and ALK-positive NSCLC as identified by the VENTANA ALK (D5F3) CDx assay. Neurologically stable patients with treated or untreated central nervous system (CNS) metastases, including leptomeningeal metastases, were eligible; patients with neurologic signs and symptoms due to CNS metastases were required to have completed whole brain radiation or gamma knife irradiation at least 14 days prior to enrollment and be clinically stable. Patients with a baseline QTc > 470 ms were ineligible.

Patients were randomized 1:1 to receive ALECENSA 600 mg orally twice daily or crizotinib 250 mg orally twice daily. Randomization was stratified by ECOG performance status (0/1 vs. 2), race (Asian vs. other races), and the presence or absence of CNS metastases at baseline. Treatment on both arms was continued until disease progression or unacceptable toxicity. The major efficacy outcome measure was progression-free survival (PFS) as determined by investigator assessment according to RECIST v1.1. Additional efficacy outcome measures were PFS as determined by independent review committee (IRC), time to CNS progression by IRC based on RECIST v1.1, objective response rate (ORR) and duration of response (DOR), and OS. Additional exploratory outcome measures were CNS objective response rate (CNS-ORR) and CNS duration of response (CNS-DOR) by IRC in patients with CNS metastases at baseline.

A total of 303 patients were randomized to ALECENSA (n=152) or crizotinib (n=151). The demographic characteristics of the study population were 56% female, median age 56 years (range: 18 to 91 years), 50% White, 46% Asian, 1% Black, and 3% other races. The majority of patients had adenocarcinoma (92%) and never smoked (63%). CNS metastases were present in 40% (n=122) of patients: of these, 43 patients had measurable CNS lesions as determined by an IRC. The ALEX study demonstrated a significant improvement in PFS. The time to cause-specific CNS progression as assessed by IRC was also significantly improved; there was a lower incidence of progression in the CNS as the first site of disease progression, alone or with concurrent systemic progression, in the ALECENSA arm (12%) as compared to the crizotinib arm (45%). Efficacy results from ALEX are summarized in Table 11 and Figure 2.

Table 11: Efficacy Results in ALEX per IRC Assessment
 | ALECENSA N=152 | Crizotinib N=151
Progression-Free Survival
Number of events (%) | 63 (41%) | 92 (61%)
Progressive disease (%) | 51 (34%) | 82 (54%)
Death (%) | 12 (8%) | 10 (7%)
Median in months (95% CI) | 25.7 (19.9, NE) | 10.4 (7.7, 14.6)
Hazard ratio (95% CI) [Stratified by race (Asian vs. other races) and CNS metastases at baseline (yes vs. no) for Cox model, log-rank test and Cochran Mantel-Haenszel test, respectively] | 0.53 (0.38, 0.73)
P-value | < 0.0001
Overall Response Rate
Overall response rate, % (95% CI) [Clopper and Pearson exact binomial 95% confidence interval.] | 79% (72, 85) | 72% (64, 79)
P-value | 0.1652
Complete response, % | 13% | 6%
Partial response, % | 66% | 66%
Duration of Response
Number of responders | n=120 | n=109
Response duration ≥6 months | 82% | 57%
Response duration ≥12 months | 64% | 36%
Response duration ≥18 months | 37% | 14%
CNS: central nervous system, ORR: overall response rate, IRC: independent review committee, CI: confidence interval, NE: not estimable.

Figure 2: Kaplan-Meier Plot of Progression-Free Survival (IRC) in ALEX

Results for PFS as determined by investigator assessment (HR=0.48 [95% CI: 0.35-0.66], stratified log-rank p<0.0001) were similar to that observed by IRC. At the data cutoff point overall survival data was not mature.

The results of prespecified exploratory analyses of CNS response rate in patients with measurable CNS lesions at baseline are summarized in Table 12.

Table 12: IRC-Assessed CNS Responses in Patients with Measurable CNS Lesions at Baseline in ALEX
 | ALECENSA | Crizotinib
CNS Tumor Response Assessment | N = 21 | N = 22
CNS Objective Response Rate, % (95% CI [Clopper and Pearson exact binomial 95% confidence interval]) | 81% (58, 95) | 50% (28,72)
Complete Response | 38% | 5%
Duration of CNS Response
Number of responders | 17 | 11
CNS response duration ≥ 12 months | 59% | 36%
IRC: Independent Review Committee; CI: Confidence Interval; NE: Not Estimable

Metastatic ALK-Positive NSCLC Previously Treated with Crizotinib

The safety and efficacy of ALECENSA were established in two single-arm, multicenter clinical trials: NP28761 (NCT01588028) and NP28673 (NCT01801111). Patients with locally advanced or metastatic ALK-positive NSCLC, who have progressed on crizotinib, with documented ALK-positive NSCLC based on an FDA-approved test, and ECOG PS of 0-2 were enrolled in both studies. Eligibility criteria permitted enrollment of patients with prior chemotherapy and prior CNS radiotherapy provided that CNS metastases were stable for at least two weeks. All patients received ALECENSA 600 mg orally twice daily. The major efficacy outcome measure in both studies was objective response rate (ORR) according to Response Evaluation Criteria in Solid Tumors (RECIST v1.1) as evaluated per Independent Review Committee (IRC). Additional outcome measures as evaluated by the IRC included duration of response (DOR), CNS ORR, and CNS DOR.

NP28761 was conducted in North America and enrolled 87 patients. Baseline demographic and disease characteristics in NP28761 were median age 54 years old (range 29 to 79, 18% 65 and over), 84% White and 8% Asian, 55% female, 35% ECOG PS 0 and 55% ECOG PS 1, 100% never or former smokers, 99% Stage IV, 94% adenocarcinoma, and 74% prior chemotherapy. The most common sites of extra-thoracic metastasis included 60% CNS (of whom 65% had received CNS radiation), 43% lymph nodes, 36% bone, and 34% liver.

NP28673 was conducted internationally and enrolled 138 patients. Baseline demographic and disease characteristics in NP28673 were median age 52 years old (range 22 to 79, 10% 65 and over), 67% White and 26% Asian, 56% female, 32% ECOG PS 0 and 59% ECOG PS 1, 98% never or former smokers, 99% Stage IV, 96% adenocarcinoma, and 80% prior chemotherapy. The most common sites of extra-thoracic metastasis included 61% CNS (of whom 73% had received CNS radiation), 51% bone, 38% lymph nodes, and 30% liver.

Efficacy results from NP28761 and NP28673 in all treated patients are summarized in Table 13. The median duration of follow-up on Study NP28761 was 4.8 months for both IRC and Investigator assessments and on Study NP28673, 10.9 months for IRC assessment and 7.0 months for Investigator assessment. All responses were partial responses.

Table 13: Efficacy Results in Studies NP28761 and NP28673
Efficacy Parameter | NP28761 (N=87) |  | NP28673 (N=138)
Efficacy Parameter | IRC [18 patients in NP28761 and 16 patients in NP28673 did not have measurable disease at baseline as per IRC assessment and were classified as non-responders in the IRC analysis.] Assessment | Investigator Assessment | IRC Assessment | Investigator Assessment
Objective Response Rate (95% CI) | 38% (28; 49) | 46% (35; 57) | 44% (36; 53) | 48% (39; 57)
Number of Responders | 33 | 40 | 61 | 66
Duration of Response, median in months (95% CI) | 7.5 (4.9, Not Estimable) | NE (4.9, Not Estimable) | 11.2 (9.6, Not Estimable) | 7.8 (7.4, 9.2)

An assessment of ORR and duration of response for CNS metastases in the subgroup of 51 patients in NP28761 and NP28673 with baseline measurable lesions in the CNS according to RECIST v1.1 are summarized in Table 14. Thirty-five (69%) patients with measurable CNS lesions had received prior brain radiation, including 25 (49%) who completed radiation treatment at least 6 months before starting treatment with ALECENSA. Responses were observed irrespective of prior brain radiation status.

Table 14: CNS Objective Response in Patients with Measurable CNS Lesions in Studies NP28761 and NP28673
Efficacy Parameter | N=51
CNS Objective Response Rate (95% CI) | 61% (46, 74)
Complete Response | 18%
Partial Response | 43%
CNS Duration of Response, median in months (95% CI) | 9.1 (5.8, Not Estimable)

16 HOW SUPPLIED/STORAGE AND HANDLING

Hard capsules, white 150 mg capsules with "ALE" printed in black ink on the cap and "150 mg" printed in black ink on the body, available in:

240 capsules per bottle: | NDC 50242-130-01

STORAGE AND HANDLING

Storage and stability: Do not store above 30°C (86°F). Store in the original container to protect from light and moisture.

17 PATIENT COUNSELING INFORMATION

Advise the patient to read the FDA-approved patient labeling (Patient Information).

Inform patients of the following:

Hepatotoxicity

Inform patients of the signs and symptoms of bilirubin and hepatic transaminase elevations. Advise patients to contact their healthcare provider immediately for signs or symptoms of bilirubin and hepatic transaminase elevations [see Warnings and Precautions (5.1)].

Interstitial Lung Disease (ILD)/Pneumonitis

Inform patients of the risks of severe ILD/pneumonitis. Advise patients to contact their healthcare provider immediately to report new or worsening respiratory symptoms [see Warnings and Precautions (5.2)].

Renal Impairment

Inform patients of the risk of severe and potentially fatal renal impairment. Advise patients to contact their healthcare provider for change in urine color, reduced urine output, or swelling in the legs and feet [see Warnings and Precautions (5.3)].

Bradycardia

Inform patients that symptoms of bradycardia including dizziness, lightheadedness, and syncope can occur while taking ALECENSA. Advise patients to contact their healthcare provider to report these symptoms and to inform their healthcare provider about the use of any heart or blood pressure medications [see Warnings and Precautions (5.4)].

Severe Myalgia/CPK Elevation

Inform patients of signs and symptoms of myalgia, including unexplained and/or persistent muscle pain, tenderness, or weakness. Advise patients to contact their healthcare provider immediately to report new or worsening symptoms of muscle pain or weakness [see Warnings and Precautions (5.5)].

Hemolytic Anemia

Advise patients to contact their healthcare provider if they develop any signs or symptoms of hemolytic anemia [see Warnings and Precautions (5.6)].

Photosensitivity

Inform patients of the signs and symptoms of photosensitivity. Advise patients to avoid prolonged sun exposure while taking ALECENSA and for at least 7 days after study drug discontinuation and to use proper protection from the sun. Advise patients to use a broad spectrum ultraviolet A (UVA)/ultraviolet B (UVB) sunscreen and lip balm (SPF ≥ 50) to help protect against potential sunburn [see Adverse Reactions (6.1)].

Embryo-Fetal Toxicity

ALECENSA can cause fetal harm if taken during pregnancy. Advise a pregnant woman and females of reproductive potential of the potential risk to a fetus [see Warnings and Precautions (5.6) and Use in Specific Populations (8.1, 8.3)].

Advise females of reproductive potential to use effective contraception during treatment with ALECENSA and for 5 weeks after the last dose of ALECENSA. Advise patients to inform their healthcare provider of a known or suspected pregnancy [see Warnings and Precautions (5.6) and Use in Specific Populations (8.1, 8.3)].

Advise male patients with female partners of reproductive potential to use effective contraception during treatment with ALECENSA and for 3 months after the last dose [see Use in Specific Populations (8.3) and Nonclinical Toxicology (13.1)].

Lactation

Advise women not to breastfeed during treatment with ALECENSA and for 1 week after the last dose [see Use in Specific Populations (8.2)].

Administration

Instruct patients to take ALECENSA twice a day. Advise patients to take ALECENSA with food and to swallow ALECENSA capsules whole [see Dosage and Administration (2.2)].

Missed Dose

Advise patients that if a dose of ALECENSA is missed or if the patient vomits after taking a dose of ALECENSA, patients should be advised not to take an extra dose, but to take the next dose at the regular time [see Dosage and Administration (2.2)].

Distributed by:
Genentech USA, Inc.
A Member of the Roche Group
1 DNA Way
South San Francisco, CA 94080-4990

ALECENSA® is a registered trademark of
Chugai Pharmaceutical Co., Ltd., Tokyo, Japan
©2024 Genentech, Inc. All rights reserved.

PATIENT INFORMATION
ALECENSA® (a-le-sen-sah)
(alectinib)
capsules

What is the most important information I should know about ALECENSA?
ALECENSA may cause serious side effects, including:

- Liver problems (hepatotoxicity). Liver problems are common with ALECENSA and can be severe. Your healthcare provider will do blood tests at least every 2 weeks for the first 3 months, and then 1 time each month and as needed during treatment with ALECENSA to check your liver function. Tell your healthcare provider right away if you get any of the following signs and symptoms:

- feeling tired
- feeling less hungry than usual
- yellowing of your skin or the whites of your eyes
- dark urine

- itchy skin
- nausea or vomiting
- pain on the right side of your stomach area
- bleeding or bruising more easily than normal

- Lung problems. ALECENSA may cause severe or life-threatening swelling (inflammation) of the lungs during treatment. Symptoms may be similar to those symptoms from lung cancer. Tell your healthcare provider right away if you have any new or worsening symptoms, including trouble breathing, shortness of breath, cough, or fever.
- Kidney problems. ALECENSA may cause severe kidney problems that can lead to death. Tell your healthcare provider right away if you have a change in the amount or color of your urine, or if you get new or worsening swelling in your legs or feet.
- Slow heartbeat (bradycardia). ALECENSA may cause very slow heartbeats that can be severe. Your healthcare provider will check your heart rate and blood pressure during treatment with ALECENSA. Tell your healthcare provider right away if you feel dizzy, lightheaded, or if you faint during treatment with ALECENSA. Tell your healthcare provider if you take any heart or blood pressure medicines.
- Severe muscle pain, tenderness, and weakness (myalgia). Muscle problems are common with ALECENSA and can be severe. Your healthcare provider will do blood tests at least every 2 weeks for the first month and as needed during treatment with ALECENSA. Tell your healthcare provider right away if you get new or worsening signs and symptoms of muscle problems, including unexplained muscle pain or muscle pain that does not go away, tenderness, or weakness.
- Breakdown of healthy red blood cells earlier than normal (hemolytic anemia). Hemolytic anemia can happen in some people who take ALECENSA. If this happens, you may not have enough healthy red blood cells. Your healthcare provider may temporarily stop ALECENSA and do blood tests, if needed, to check for this problem. If you develop hemolytic anemia, your healthcare provider may either restart you on ALECENSA at a lower dose when the hemolytic anemia goes away, or may stop your treatment with ALECENSA. Tell your healthcare provider right away if you experience yellow skin (jaundice), weakness or dizziness, or shortness of breath.

See "What are the possible side effects of ALECENSA?" for more information about side effects.

What is ALECENSA?
ALECENSA is a prescription medicine used to treat adults with non-small cell lung cancer (NSCLC) that is caused by an abnormal anaplastic lymphoma kinase (ALK) gene:

- to help prevent your lung cancer from coming back after your tumor has been removed by surgery (adjuvant), or
- as treatment when your lung cancer has spread to other parts of your body (metastatic).

Your healthcare provider will perform a test to make sure that ALECENSA is right for you.
It is not known if ALECENSA is safe and effective in children.

Before you take ALECENSA, tell your healthcare provider about all of your medical conditions, including if you:

- have liver problems
- have lung or breathing problems
- have a slow heartbeat
- are pregnant or plan to become pregnant. ALECENSA can harm your unborn baby.
  Females who are able to become pregnant:
  - Your healthcare provider will do a test to see if you are pregnant before starting treatment with ALECENSA.
  - You should use effective birth control (contraception) during treatment with ALECENSA and for 5 weeks after the last dose of ALECENSA.
  - Tell your healthcare provider right away if you become pregnant during treatment with ALECENSA or think you may be pregnant.
  Males who have female partners that are able to become pregnant should use effective birth control (contraception) during treatment with ALECENSA and for 3 months after the last dose of ALECENSA.
- are breastfeeding or plan to breastfeed. It is not known if ALECENSA passes into your breast milk. Do not breastfeed during treatment with ALECENSA and for 1 week after the last dose of ALECENSA. Talk to your healthcare provider about the best way to feed your baby during this time.

Tell your healthcare provider about all the medicines you take, including prescription medicines, over-the-counter medicines, vitamins, or herbal supplements.

How should I take ALECENSA?

- Take ALECENSA exactly as your healthcare provider tells you to take it. Do not change your dose or stop taking ALECENSA unless your healthcare provider tells you to.
- Your healthcare provider may change your dose, temporarily stop, or permanently stop treatment with ALECENSA if you have side effects.
- Take ALECENSA 2 times a day.
- Take ALECENSA with food.
- Swallow ALECENSA capsules whole. Do not open or dissolve the capsule contents.
- If you miss a dose of ALECENSA, do not take the missed dose. Take your next dose at your regular time.
- If you vomit after taking a dose of ALECENSA, do not take an extra dose. Take your next dose at your regular time.

What should I avoid while taking ALECENSA?
Avoid spending time in the sunlight during treatment with ALECENSA and for 7 days after the last dose of ALECENSA. Your skin may be sensitive to the sun (photosensitivity) and you may burn more easily and get severe sunburns. Use sun protecting measures, such as sunscreen and lip balm with an SPF 50 or greater to help protect against sunburn.

What are the possible side effects of ALECENSA?
ALECENSA may cause serious side effects, including:

- See "What is the most important information I should know about ALECENSA?"

The most common side effects of ALECENSA include:

- constipation
- tiredness
- swelling in your hands, feet, ankles, face and eyelids

- rash
- cough

These are not all of the possible side effects of ALECENSA. For more information, ask your healthcare provider or pharmacist.
Call your doctor for medical advice about side effects. You may report side effects to FDA at 1-800-FDA-1088.

How should I store ALECENSA?

- Do not store ALECENSA at temperatures above 86°F (30°C).
- Store ALECENSA capsules in the original container.
- Keep ALECENSA capsules dry and away from light.

Keep ALECENSA and all medicines out of the reach of children.

General information about the safe and effective use of ALECENSA.
Medicines are sometimes prescribed for purposes other than those listed in a Patient Information leaflet. Do not use ALECENSA for a condition for which it was not prescribed. Do not give ALECENSA to other people, even if they have the same symptoms that you have. It may harm them. You can ask your pharmacist or healthcare provider for information about ALECENSA that is written for health professionals.

What are the ingredients in ALECENSA?
Active ingredient: alectinib
Inactive ingredients: lactose monohydrate, hydroxypropylcellulose, sodium lauryl sulfate, magnesium stearate and carboxymethylcellulose calcium. Capsule shell contains: hypromellose, carrageenan, potassium chloride, titanium dioxide, corn starch, and carnauba wax. Printing ink contains: red iron oxide (E172), yellow iron oxide (E172), FD&C Blue No. 2 aluminum lake (E132), carnauba wax, white shellac, and glyceryl monooleate.
Distributed by: Genentech, Inc., A Member of the Roche Group, 1 DNA Way, South San Francisco, CA 94080-4990
ALECENSA® is a registered trademark of Chugai Pharmaceutical Co., Ltd., Tokyo, Japan
©2024 Genentech, Inc.
For more information, go to www.ALECENSA.com or call 1-800-253-2367.

This Patient Information has been approved by the U.S. Food and Drug Administration.

Revised: 04/2024

PRINCIPAL DISPLAY PANEL - 150 mg Capsule Bottle Carton

NDC 50242-130-01

Alecensa®
(alectinib)
capsules

150 mg

Each capsule contains 150 mg of alectinib
(equivalent to 161.33 mg alectinib HCl).

Rx only

240 capsules

Genentech

11008914